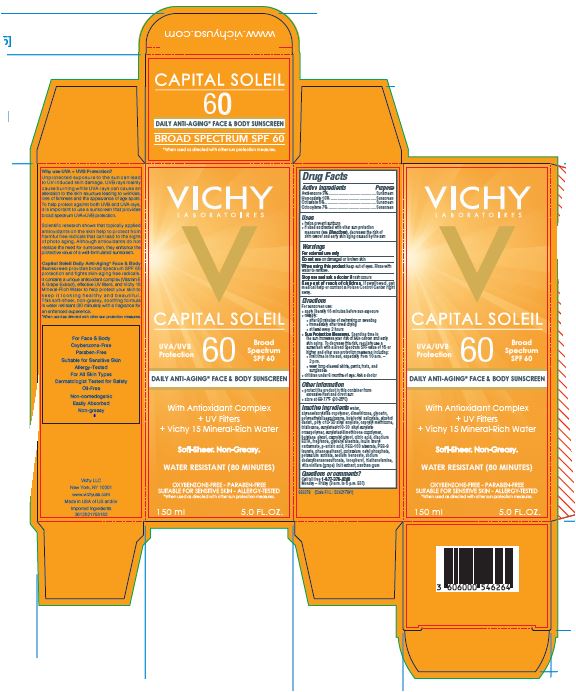 DRUG LABEL: Vichy Laboratoires Capital Soleil 60 Daily AntiAging Face and Body Sunscreen Broad Spectrum SPF 60 Water Resistant 80 Minutes
NDC: 49967-546 | Form: LOTION
Manufacturer: L’Oreal USA Products Inc
Category: otc | Type: HUMAN OTC DRUG LABEL
Date: 20231227

ACTIVE INGREDIENTS: AVOBENZONE 30 mg/1 mL; HOMOSALATE 100 mg/1 mL; OCTISALATE 50 mg/1 mL; OCTOCRYLENE 70 mg/1 mL
INACTIVE INGREDIENTS: WATER; STYRENE/ACRYLAMIDE COPOLYMER (500000 MW); DIMETHICONE; GLYCERIN; POLYMETHYLSILSESQUIOXANE (4.5 MICRONS); BUTYLOCTYL SALICYLATE; ALCOHOL; CAPRYLYL TRISILOXANE; TRISILOXANE; CARBOMER INTERPOLYMER TYPE A (ALLYL SUCROSE CROSSLINKED); BUTYLENE GLYCOL; CAPRYLYL GLYCOL; CITRIC ACID MONOHYDRATE; EDETATE DISODIUM; GLYCERYL MONOSTEARATE; P-ANISIC ACID; PEG-100 STEARATE; PEG-8 LAURATE; PHENOXYETHANOL; POTASSIUM CETYL PHOSPHATE; POTASSIUM SORBATE; SODIUM BENZOATE; SODIUM DODECYLBENZENESULFONATE; TOCOPHEROL; TROLAMINE; WINE GRAPE; XANTHAN GUM

Drug Facts

Active ingredients

Avobenzone 3%

Homosalate 10%

Octisalate 5%

Octocrylene 7%

Purpose

Sunscreen

Uses

- helps prevent sunburn
- if used as directed with other sun protection measures (see Directions), decreases the risk of skin cancer and early skin aging caused by the sun

Warnings

For external use only

Do not use

on damaged or broken skin

When using this product

keep out of eyes. Rinse with water to remove.

Stop use and ask a doctor if

rash occurs

Keep out of reach of children.

If swallowed, get medical help or contact a Poison Control Center right away.

Directions

For sunscreen use:

● apply liberally 15 minutes before sun exposure

● reapply:

● after 80 minutes of swimming or sweating

● immediately after towel drying

● at least every 2 hours

● Sun Protection Measures. Spending time in the sun increases your risk of skin cancer and early skin aging. To decrease this risk, regularly use a sunscreen with a Broad Spectrum SPF value of 15 or higher and other sun protection measures including:

● limit time in the sun, especially from 10 a.m. – 2 p.m.

● wear long-sleeved shirts, pants, hats, and sunglasses

● children under 6 months of age: Ask a doctor

Other information

protect the product in this container from excessive heat and direct sun

Inactive ingredients

water, styrene/acrylates copolymer, dimethicone, glycerin, polymethylsilsesquioxane, butyloctyl salicylate, alcohol denat., poly c10-30 alkyl acrylate, caprylyl methicone, trisiloxane, acrylates/c10-30 alkyl acrylate crosspolymer, acrylates/dimethicone copolymer, butylene glycol, caprylyl glycol, citric acid, disodium EDTA, fragrance, glyceryl stearate, inulin lauryl carbamate, p-anisic acid, PEG-100 stearate, PEG-8 laurate, phenoxyethanol, potassium cetyl phosphate, potassium sorbate, sodium benzoate, sodium dodecylbenzenesulfonate, tocopherol, triethanolamine, vitis vinifera (grape) fruit extract, xanthan gum

Questions or comments?

Call toll free 1-877-378-4249

Monday - Friday (9 a.m. to 5 p.m. EST)